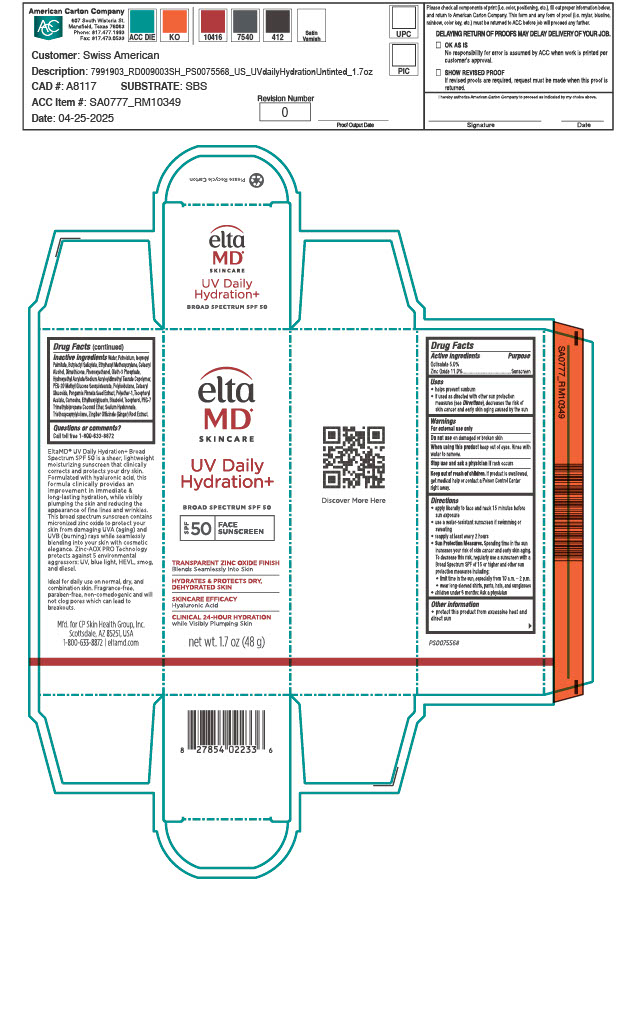 DRUG LABEL: EltaMD UV Daily Hydration
NDC: 72043-6813 | Form: LOTION
Manufacturer: CP Skin Health Group, Inc.
Category: otc | Type: HUMAN OTC DRUG LABEL
Date: 20250815

ACTIVE INGREDIENTS: OCTISALATE 50 g/1000 g; ZINC OXIDE 110 g/1000 g
INACTIVE INGREDIENTS: WATER; PETROLATUM; ISOPROPYL PALMITATE; BUTYLOCTYL SALICYLATE; ETHYLHEXYL METHOXYCRYLENE; CETEARYL ALCOHOL; DIMETHICONE; PHENOXYETHANOL; OLETH-3 PHOSPHATE; HYDROXYETHYL ACRYLATE/SODIUM ACRYLOYLDIMETHYL TAURATE COPOLYMER (100000 MPA.S AT 1.5%); PEG-20 METHYL GLUCOSE SESQUISTEARATE; POLYISOBUTYLENE (1000 MW); CETEARYL GLUCOSIDE; PONGAMIA PINNATA SEED; POLYETHER-1 (2800 MPA.S); CARNOSINE; ETHYLHEXYLGLYCERIN; BISABOLOL; TOCOPHEROL; PEG-7 TRIMETHYLOLPROPANE COCONUT ETHER; PHOSPHORIC ACID; SODIUM HYALURONATE; CITRIC ACID; CANOLA OIL; TRIETHOXYCAPRYLYLSILANE; ZINGIBER OFFICINALE (GINGER) ROOT OIL; .ALPHA.-TOCOPHEROL ACETATE, DL-

EltaMD UV Daily Hydration

Warnings

For external use only. Do not use on damaged or broken skin. When using this product keep out of eyes. Rinse with water to remove. Stop use and ask a physician if rash occurs. If product is swallowed get medical help or contact a Poison Control Center right away.

Active Ingredients

Octisalate 5.0% Sunscreen
Zinc Oxide 11.0% Sunscreen

Indications and Usage

Helps prevent sunburn. If used as directed with other sun protection measure (See Directions), decreases the risk of skin cancer and early skin aging caused by the sun.

KEEP OUT OF REACH OF CHILDREN

Purpose

Sunscreen

Directions

Apply liberally 15 minutes before sun exposure. [Use a water-resistant sunscreen if swimming or sweating. Reapply at least every 2 hours.] [Reapply: after 80 minutes of swimming or sweating, immediately after towel drying and at least every 2 hours.] Sun Protection Measures: Spending time in the sun increases your risk of skin cancer and early skin aging. To decrease this risk, regularly use a sunscreen with a broad-spectrum SPF of 15 or higher and other sun protection measures including: limit time in the sun, especially from 10 am to 2 pm. Wear long-sleeve shirts, pants, hats, and sunglasses. Children under 6 months: ask a physician.

Other Information

Protect this product from excessive heat and direct sun.

Inactive Ingredients

water, petrolatum, isopropyl palmitate, butyloctyl salicylate, ethylhexyl methocycrylene, cetearyl alcohol, diemthicone, phenoxyethanol, oleth-3 phosphate, hydroxyethyl acrylate/sodium acryloyldimethyl taurate copolymer, PEG-20 methyl glycose sesquisearate, polyisobutene, cetearyl glycoside, pongamia pinnata seed extract, polyether-1 tocopheryl acetate, carnosine, ethylhexylglycerin, bisabolol, tocopherol, PEG-7 trimethylolpropane coconut ether, phospohoric acid, sodium hyaluronate, citric acid, canola oil, triethoxycprylylsilane, zingiber officinale (ginger) root extract

Questions or Comments?

Call toll free 1-800-633-8872